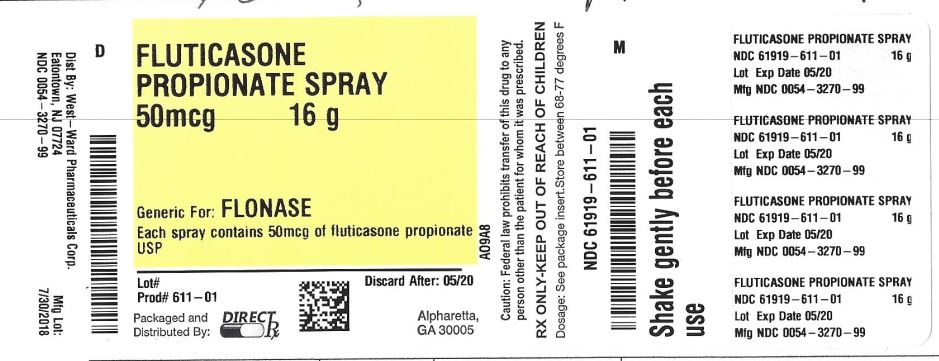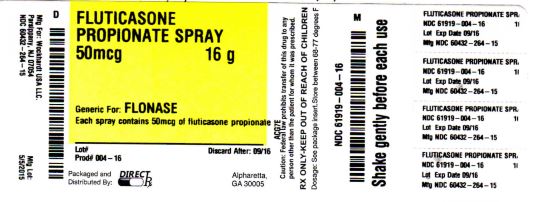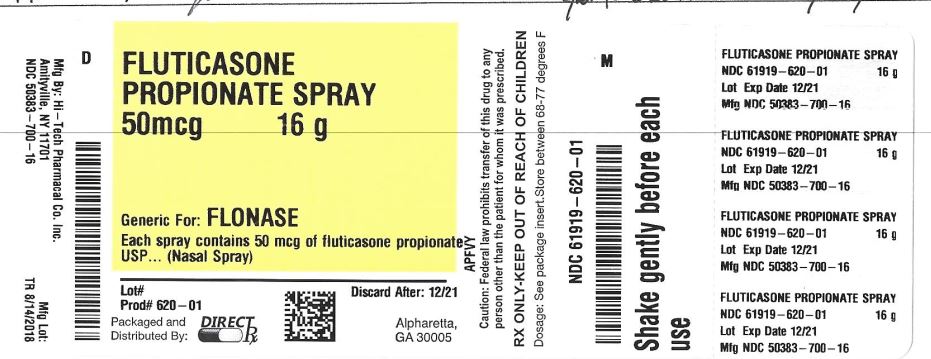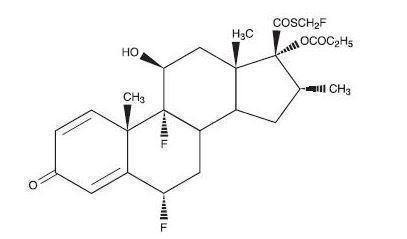 DRUG LABEL: FLUTICASONE
NDC: 61919-611 | Form: SPRAY, METERED
Manufacturer: Direct RX
Category: prescription | Type: HUMAN PRESCRIPTION DRUG LABEL
Date: 20190409

ACTIVE INGREDIENTS: FLUTICASONE PROPIONATE 50 ug/1 1
INACTIVE INGREDIENTS: MICROCRYSTALLINE CELLULOSE; DEXTROSE, UNSPECIFIED FORM; POLYSORBATE 80; CARBOXYMETHYLCELLULOSE SODIUM, UNSPECIFIED FORM; BENZALKONIUM CHLORIDE

FLUTICASONE PROPIONATE SPRAY

DESCRIPTION SECTION

Fluticasone propionate, the active component of Fluticasone Propionate Nasal Spray, USP is a synthetic corticosteroid having the chemical name S-(fluoromethyl)6α,9-difluoro-11β-17-dihydroxy-16α-methyl-3-oxoandrosta-1,4-diene-17β-carbothioate, 17-propionate and the following chemical structure:

Fluticasone propionate is a white to off-white powder with a molecular weight of 500.6, and the molecular formula is C25H31F3O5S. It is practically insoluble in water, freely soluble in dimethyl sulfoxide and dimethylformamide, and slightly soluble in methanol and 95% ethanol.

Fluticasone Propionate Nasal Spray, USP 50 mcg is an aqueous suspension of microfine fluticasone propionate for topical administration to the nasal mucosa by means of a metering, atomizing spray pump. Fluticasone Propionate Nasal Spray, USP also contains microcrystalline cellulose and carboxymethylcellulose sodium, dextrose, 0.02% w/w benzalkonium chloride, polysorbate 80, and 0.25% w/w phenylethyl alcohol, and has a pH between 5 and 7.

It is necessary to prime the pump before first use or after a period of non-use (1 week or more). After initial priming (6 actuations), each actuation delivers 50 mcg of fluticasone propionate in 100 mg of formulation through the nasal adapter. Each 16-g bottle of Fluticasone Propionate Nasal Spray, USP provides 120 metered sprays. After 120 metered sprays, the amount of fluticasone propionate delivered per actuation may not be consistent and the unit should be discarded.

CLINICAL PHARMACOLOGY SECTION

Mechanism of Action

Fluticasone propionate is a synthetic, trifluorinated corticosteroid with anti-inflammatory activity. In vitro dose response studies on a cloned human glucocorticoid receptor system involving binding and gene expression afforded 50% responses at 1.25 and 0.17 nM concentrations, respectively. Fluticasone propionate was 3-fold to 5-fold more potent than dexamethasone in these assays. Data from the McKenzie vasoconstrictor assay in man also support its potent glucocorticoid activity.

In preclinical studies, fluticasone propionate revealed progesterone-like activity similar to the natural hormone. However, the clinical significance of these findings in relation to the low plasma levels (see Pharmacokinetics) is not known.

The precise mechanism through which fluticasone propionate affects allergic rhinitis symptoms is not known. Corticosteroids have been shown to have a wide range of effects on multiple cell types (e.g., mast cells, eosinophils, neutrophils, macrophages, and lymphocytes) and mediators (e.g., histamine, eicosanoids, leukotrienes, and cytokines) involved in inflammation. In 7 trials in adults, Fluticasone Propionate Nasal Spray, USP has decreased nasal mucosal eosinophils in 66% (35% for placebo) of patients and basophils in 39% (28% for placebo) of patients. The direct relationship of these findings to long-term symptom relief is not known.

Fluticasone Propionate Nasal Spray, USP like other corticosteroids, is an agent that does not have an immediate effect on allergic symptoms. A decrease in nasal symptoms has been noted in some patients 12 hours after initial treatment with Fluticasone Propionate Nasal Spray, USP. Maximum benefit may not be reached for several days. Similarly, when corticosteroids are discontinued, symptoms may not return for several days.

PharmacokineticsAbsorption

The activity of Fluticasone Propionate Nasal Spray, USP is due to the parent drug, fluticasone propionate. Indirect calculations indicate that fluticasone propionate delivered by the intranasal route has an absolute bioavailability averaging less than 2%. After intranasal treatment of patients with allergic rhinitis for 3 weeks, fluticasone propionate plasma concentrations were above the level of detection (50 pg/mL) only when recommended doses were exceeded and then only in occasional samples at low plasma levels. Due to the low bioavailability by the intranasal route, the majority of the pharmacokinetic data was obtained via other routes of administration. Studies using oral dosing of radiolabeled drug have demonstrated that fluticasone propionate is highly extracted from plasma and absorption is low. Oral bioavailability is negligible, and the majority of the circulating radioactivity is due to an inactive metabolite.

Distribution

Following intravenous administration, the initial disposition phase for fluticasone propionate was rapid and consistent with its high lipid solubility and tissue binding. The volume of distribution averaged 4.2 L/kg.

The percentage of fluticasone propionate bound to human plasma proteins averaged 91% with no obvious concentration relationship. Fluticasone propionate is weakly and reversibly bound to erythrocytes and freely equilibrates between erythrocytes and plasma. Fluticasone propionate is not significantly bound to human transcortin.

Metabolism

The total blood clearance of fluticasone propionate is high (average, 1,093 mL/min), with renal clearance accounting for less than 0.02% of the total. The only circulating metabolite detected in man is the 17β-carboxylic acid derivative of fluticasone propionate, which is formed through the cytochrome P450 3A4 pathway. This inactive metabolite had less affinity (approximately 1/2,000) than the parent drug for the glucocorticoid receptor of human lung cytosol in vitro and negligible pharmacological activity in animal studies. Other metabolites detected in vitro using cultured human hepatoma cells have not been detected in man.

Elimination

Following intravenous dosing, fluticasone propionate showed polyexponential kinetics and had a terminal elimination half-life of approximately 7.8 hours. Less than 5% of a radiolabeled oral dose was excreted in the urine as metabolites, with the remainder excreted in the feces as parent drug and metabolites.

Special Populations

Fluticasone Propionate Nasal Spray, USP was not studied in any special populations, and no gender-specific pharmacokinetic data have been obtained.

Drug Interactions

Fluticasone propionate is a substrate of cytochrome P450 3A4. Coadministration of fluticasone propionate and the highly potent cytochrome P450 3A4 inhibitor ritonavir is not recommended based upon a multiple-dose, crossover drug interaction study in 18 healthy subjects. Fluticasone propionate aqueous nasal spray (200 mcg once daily) was coadministered for 7 days with ritonavir (100 mg twice daily). Plasma fluticasone propionate concentrations following fluticasone propionate aqueous nasal spray alone were undetectable (<10 pg/mL) in most subjects, and when concentrations were detectable peak levels (Cmax averaged 11.9 pg/mL [range, 10.8 to 14.1 pg/mL] and AUC(0–τ) averaged 8.43 pg∙hr/mL [range, 4.2 to 18.8 pg∙hr/mL]). Fluticasone propionate Cmax and AUC(0–τ) increased to 318 pg/mL (range, 110 to 648 pg/mL) and 3,102.6 pg∙hr/mL (range, 1,207.1 to 5,662.0 pg∙hr/mL), respectively, after coadministration of ritonavir with fluticasone propionate aqueous nasal spray. This significant increase in plasma fluticasone propionate exposure resulted in a significant decrease (86%) in plasma cortisol area under the plasma concentration versus time curve (AUC).

Caution should be exercised when other potent cytochrome P450 3A4 inhibitors are coadministered with fluticasone propionate. In a drug interaction study, coadministration of orally inhaled fluticasone propionate (1,000 mcg) and ketoconazole (200 mg once daily) resulted in increased fluticasone propionate exposure and reduced plasma cortisol AUC, but had no effect on urinary excretion of cortisol.

In another multiple-dose drug interaction study, coadministration of orally inhaled fluticasone propionate (500 mcg twice daily) and erythromycin (333 mg 3 times daily) did not affect fluticasone propionate pharmacokinetics.

Pharmacodynamics

In a trial to evaluate the potential systemic and topical effects of Fluticasone Propionate Nasal Spray, USP on allergic rhinitis symptoms, the benefits of comparable drug blood levels produced by Fluticasone Propionate Nasal Spray, USP and oral fluticasone propionate were compared. The doses used were 200 mcg of Fluticasone Propionate Nasal Spray, USP, the nasal spray vehicle (plus oral placebo), and 5 and 10 mg of oral fluticasone propionate (plus nasal spray vehicle) per day for 14 days. Plasma levels were undetectable in the majority of patients after intranasal dosing, but present at low levels in the majority after oral dosing. Fluticasone Propionate Nasal Spray, USP was significantly more effective in reducing symptoms of allergic rhinitis than either the oral fluticasone propionate or the nasal vehicle. This trial demonstrated that the therapeutic effect of Fluticasone Propionate Nasal Spray, USP can be attributed to the topical effects of fluticasone propionate.

In another trial, the potential systemic effects of Fluticasone Propionate Nasal Spray, USP on the hypothalamic-pituitary-adrenal (HPA) axis were also studied in allergic patients. Fluticasone Propionate Nasal Spray, USP given as 200 mcg once daily or 400 mcg twice daily was compared with placebo or oral prednisone 7.5 or 15 mg given in the morning. Fluticasone Propionate Nasal Spray, USP at either dose for 4 weeks did not affect the adrenal response to 6-hour cosyntropin stimulation, while both doses of oral prednisone significantly reduced the response to cosyntropin.

Clinical Trials

A total of 13 randomized, double-blind, parallel-group, multicenter, vehicle placebo-controlled clinical trials were conducted in the United States in adults and pediatric patients (4 years of age and older) to investigate regular use of Fluticasone Propionate Nasal Spray, USP in patients with seasonal or perennial allergic rhinitis. The trials included 2,633 adults (1,439 men and 1,194 women) with a mean age of 37 (range, 18 to 79 years). A total of 440 adolescents (405 boys and 35 girls), mean age of 14 (range, 12 to 17 years), and 500 children (325 boys and 175 girls), mean age of 9 (range, 4 to 11 years) were also studied. The overall racial distribution was 89% white, 4% black, and 7% other. These trials evaluated the total nasal symptom scores (TNSS) that included rhinorrhea, nasal obstruction, sneezing, and nasal itching in known allergic patients who were treated for 2 to 24 weeks. Subjects treated with Fluticasone Propionate Nasal Spray, USP exhibited significantly greater decreases in TNSS than vehicle placebo-treated patients. Nasal mucosal basophils and eosinophils were also reduced at the end of treatment in adult studies; however, the clinical significance of this decrease is not known.

There were no significant differences between fluticasone propionate regimens whether administered as a single daily dose of 200 mcg (two 50-mcg sprays in each nostril) or as 100 mcg (one 50-mcg spray in each nostril) twice daily in 6 clinical trials. A clear dose response could not be identified in clinical trials. In 1 trial, 200 mcg/day was slightly more effective than 50 mcg/day during the first few days of treatment; thereafter, no difference was seen.

Two randomized, double-blind, parallel-group, multicenter, vehicle placebo-controlled 28-day trials were conducted in the United States in 732 patients (243 given fluticasone propionate) 12 years of age and older to investigate "as-needed" use of Fluticasone Propionate Nasal Spray, USP (200 mcg) in patients with seasonal allergic rhinitis. Patients were instructed to take the study medication only on days when they thought they needed the medication for symptom control, not to exceed 2 sprays per nostril on any day, and not more than once daily. "As-needed" use was prospectively defined as average use of study medication no more than 75% of study days. Average use of study medications was 57% to 70% of days for all treatment arms. The studies demonstrated significantly greater reduction in TNSS (sum of nasal congestion, rhinorrhea, sneezing, and nasal itching) with Fluticasone Propionate Nasal Spray, USP 200 mcg compared to placebo. The relative difference in efficacy with as-needed use as compared to regularly administered doses was not studied.

Three randomized, double-blind, parallel-group, vehicle placebo-controlled trials were conducted in 1,191 patients to investigate regular use of Fluticasone Propionate Nasal Spray, USP in patients with perennial nonallergic rhinitis. These trials evaluated the patient-rated TNSS (nasal obstruction, postnasal drip, rhinorrhea) in patients treated for 28 days of double-blind therapy and in 1 of the 3 trials for 6 months of open-label treatment. Two of these trials demonstrated that patients treated with Fluticasone Propionate Nasal Spray, USP at a dose of 100 mcg twice daily exhibited statistically significant decreases in TNSS compared with patients treated with vehicle.

Individualization of Dosage

Patients should use Fluticasone Propionate Nasal Spray, USP at regular intervals for optimal effect.

Adult patients may be started on a 200-mcg once-daily regimen (two 50-mcg sprays in each nostril once daily). An alternative 200-mcg/day dosage regimen can be given as 100 mcg twice daily (one 50-mcg spray in each nostril twice daily).

Individual patients will experience a variable time to onset and different degree of symptom relief. In 4 randomized, double-blind, vehicle placebo-controlled, parallel-group allergic rhinitis studies and 2 studies of patients in an outdoor "park" setting (park studies), a decrease in nasal symptoms in treated subjects compared to placebo was shown to occur as soon as 12 hours after treatment with a 200-mcg dose of Fluticasone Propionate Nasal Spray, USP. Maximum effect may take several days. Regular-use patients who have responded may be able to be maintained (after 4 to 7 days) on 100 mcg/day (1 spray in each nostril once daily).

Some patients (12 years of age and older) with seasonal allergic rhinitis may find as-needed use of Fluticasone Propionate Nasal Spray, USP (not to exceed 200 mcg daily) effective for symptom control (see Clinical Trials). Greater symptom control may be achieved with scheduled regular use. Efficacy of as-needed use of Fluticasone Propionate Nasal Spray, USP has not been studied in pediatric patients under 12 years of age with seasonal allergic rhinitis, or patients with perennial allergic or nonallergic rhinitis.

Pediatric patients (4 years of age and older) should be started with 100 mcg (1 spray in each nostril once daily). Treatment with 200 mcg (2 sprays in each nostril once daily or 1 spray in each nostril twice daily) should be reserved for pediatric patients not adequately responding to 100 mcg daily. Once adequate control is achieved, the dosage should be decreased to 100 mcg (1 spray in each nostril) daily.

Maximum total daily doses should not exceed 2 sprays in each nostril (total dose, 200 mcg/day). There is no evidence that exceeding the recommended dose is more effective.

INDICATIONS & USAGE SECTION

Fluticasone Propionate Nasal Spray, USP is indicated for the management of the nasal symptoms of seasonal and perennial allergic and nonallergic rhinitis in adults and pediatric patients 4 years of age and older.

Safety and effectiveness of Fluticasone Propionate Nasal Spray, USP in children below 4 years of age have not been adequately established.

CONTRAINDICATIONS SECTION

Fluticasone Propionate Nasal Spray, USP is contraindicated in patients with a hypersensitivity to any of its ingredients.

WARNINGS SECTION

The replacement of a systemic corticosteroid with a topical corticosteroid can be accompanied by signs of adrenal insufficiency, and in addition some patients may experience symptoms of withdrawal, e.g., joint and/or muscular pain, lassitude, and depression. Patients previously treated for prolonged periods with systemic corticosteroids and transferred to topical corticosteroids should be carefully monitored for acute adrenal insufficiency in response to stress. In those patients who have asthma or other clinical conditions requiring long-term systemic corticosteroid treatment, too rapid a decrease in systemic corticosteroids may cause a severe exacerbation of their symptoms.

The concomitant use of intranasal corticosteroids with other inhaled corticosteroids could increase the risk of signs or symptoms of hypercorticism and/or suppression of the HPA axis.

A drug interaction study in healthy subjects has shown that ritonavir (a highly potent cytochrome P450 3A4 inhibitor) can significantly increase plasma fluticasone propionate exposure, resulting in significantly reduced serum cortisol concentrations (see CLINICAL PHARMACOLOGY: Drug Interactions and PRECAUTIONS: Drug Interactions). During postmarketing use, there have been reports of clinically significant drug interactions in patients receiving fluticasone propionate and ritonavir, resulting in systemic corticosteroid effects including Cushing syndrome and adrenal suppression. Therefore, coadministration of fluticasone propionate and ritonavir is not recommended unless the potential benefit to the patient outweighs the risk of systemic corticosteroid side effects.

Persons who are using drugs that suppress the immune system are more susceptible to infections than healthy individuals. Chickenpox and measles, for example, can have a more serious or even fatal course in susceptible children or adults using corticosteroids. In children or adults who have not had these diseases or been properly immunized, particular care should be taken to avoid exposure. How the dose, route, and duration of corticosteroid administration affect the risk of developing a disseminated infection is not known. The contribution of the underlying disease and/or prior corticosteroid treatment to the risk is also not known. If exposed to chickenpox, prophylaxis with varicella zoster immune globulin (VZIG) may be indicated. If exposed to measles, prophylaxis with pooled intramuscular immunoglobulin (IG) may be indicated. (See the respective package inserts for complete VZIG and IG prescribing information.) If chickenpox develops, treatment with antiviral agents may be considered.

Avoid spraying in eyes.

PRECAUTIONS SECTION

General

Intranasal corticosteroids may cause a reduction in growth velocity when administered to pediatric patients (see PRECAUTIONS: Pediatric Use).

Rarely, immediate hypersensitivity reactions or contact dermatitis may occur after the administration of Fluticasone Propionate Nasal Spray, USP. Rare instances of wheezing, nasal septum perforation, cataracts, glaucoma, and increased intraocular pressure have been reported following the intranasal application of corticosteroids, including fluticasone propionate.

Use of excessive doses of corticosteroids may lead to signs or symptoms of hypercorticism and/or suppression of HPA function.

Although systemic effects have been minimal with recommended doses of Fluticasone Propionate Nasal Spray, USP potential risk increases with larger doses. Therefore, larger than recommended doses of Fluticasone Propionate Nasal Spray, USP should be avoided.

When used at higher than recommended doses or in rare individuals at recommended doses, systemic corticosteroid effects such as hypercorticism and adrenal suppression may appear. If such changes occur, the dosage of Fluticasone Propionate Nasal Spray, USP should be discontinued slowly consistent with accepted procedures for discontinuing oral corticosteroid therapy.

In clinical studies with fluticasone propionate administered intranasally, the development of localized infections of the nose and pharynx with Candida albicans has occurred only rarely. When such an infection develops, it may require treatment with appropriate local therapy and discontinuation of treatment with Fluticasone Propionate Nasal Spray, USP. Patients using Fluticasone Propionate Nasal Spray, USP over several months or longer should be examined periodically for evidence of Candida infection or other signs of adverse effects on the nasal mucosa.

Intranasal corticosteroids should be used with caution, if at all, in patients with active or quiescent tuberculous infections of the respiratory tract; untreated local or systemic fungal or bacterial infections; systemic viral or parasitic infections; or ocular herpes simplex.

Because of the inhibitory effect of corticosteroids on wound healing, patients who have experienced recent nasal septal ulcers, nasal surgery, or nasal trauma should not use a nasal corticosteroid until healing has occurred.

Information for Patients

Patients being treated with Fluticasone Propionate Nasal Spray, USP should receive the following information and instructions. This information is intended to aid them in the safe and effective use of this medication. It is not a disclosure of all possible adverse or intended effects.

Patients should be warned to avoid exposure to chickenpox or measles and, if exposed, to consult their physician without delay.

Patients should use Fluticasone Propionate Nasal Spray, USP at regular intervals for optimal effect. Some patients (12 years of age and older) with seasonal allergic rhinitis may find as-needed use of 200 mcg once daily effective for symptom control (see Clinical Trials).

A decrease in nasal symptoms may occur as soon as 12 hours after starting therapy with Fluticasone Propionate Nasal Spray, USP. Results in several clinical trials indicate statistically significant improvement within the first day or two of treatment; however, the full benefit of Fluticasone Propionate Nasal Spray, USP may not be achieved until treatment has been administered for several days. The patient should not increase the prescribed dosage but should contact the physician if symptoms do not improve or if the condition worsens.

For the proper use of Fluticasone Propionate Nasal Spray, USP and to attain maximum improvement, the patient should read and follow carefully the patient's instructions accompanying the product.

Drug Interactions

Fluticasone propionate is a substrate of cytochrome P450 3A4. A drug interaction study with fluticasone propionate aqueous nasal spray in healthy subjects has shown that ritonavir (a highly potent cytochrome P450 3A4 inhibitor) can significantly increase plasma fluticasone propionate exposure, resulting in significantly reduced serum cortisol concentrations (see CLINICAL PHARMACOLOGY: Drug Interactions). During postmarketing use, there have been reports of clinically significant drug interactions in patients receiving fluticasone propionate and ritonavir, resulting in systemic corticosteroid effects including Cushing syndrome and adrenal suppression. Therefore, coadministration of fluticasone propionate and ritonavir is not recommended unless the potential benefit to the patient outweighs the risk of systemic corticosteroid side effects.

In a placebo-controlled, crossover study in 8 healthy volunteers, coadministration of a single dose of orally inhaled fluticasone propionate (1,000 mcg; 5 times the maximum daily intranasal dose) with multiple doses of ketoconazole (200 mg) to steady state resulted in increased plasma fluticasone propionate exposure, a reduction in plasma cortisol AUC, and no effect on urinary excretion of cortisol. Caution should be exercised when Fluticasone Propionate Nasal Spray, USP is coadministered with ketoconazole and other known potent cytochrome P450 3A4 inhibitors.

Carcinogenesis, Mutagenesis, Impairment of Fertility

Fluticasone propionate demonstrated no tumorigenic potential in mice at oral doses up to 1,000 mcg/kg (approximately 20 times the maximum recommended daily intranasal dose in adults and approximately 10 times the maximum recommended daily intranasal dose in children on a mcg/m2 basis) for 78 weeks or in rats at inhalation doses up to 57 mcg/kg (approximately 2 times the maximum recommended daily intranasal dose in adults and approximately equivalent to the maximum recommended daily intranasal dose in children on a mcg/m2 basis) for 104 weeks.

Fluticasone propionate did not induce gene mutation in prokaryotic or eukaryotic cells in vitro. No significant clastogenic effect was seen in cultured human peripheral lymphocytes in vitro or in the mouse micronucleus test.

No evidence of impairment of fertility was observed in reproductive studies conducted in male and female rats at subcutaneous doses up to 50 mcg/kg (approximately 2 times the maximum recommended daily intranasal dose in adults on a mcg/m2 basis). Prostate weight was significantly reduced at a subcutaneous dose of 50 mcg/kg.

PregnancyTeratogenic EffectsPregnancy Category C

Subcutaneous studies in the mouse and rat at 45 and 100 mcg/kg, respectively (approximately equivalent to and 4 times the maximum recommended daily intranasal dose in adults on a mcg/m2 basis, respectively) revealed fetal toxicity characteristic of potent corticosteroid compounds, including embryonic growth retardation, omphalocele, cleft palate, and retarded cranial ossification.

In the rabbit, fetal weight reduction and cleft palate were observed at a subcutaneous dose of 4 mcg/kg (less than the maximum recommended daily intranasal dose in adults on a mcg/m2 basis). However, no teratogenic effects were reported at oral doses up to 300 mcg/kg (approximately 25 times the maximum recommended daily intranasal dose in adults on a mcg/m2 basis) of fluticasone propionate to the rabbit. No fluticasone propionate was detected in the plasma in this study, consistent with the established low bioavailability following oral administration (see CLINICAL PHARMACOLOGY).

Fluticasone propionate crossed the placenta following oral administration of 100 mcg/kg to rats or 300 mcg/kg to rabbits (approximately 4 and 25 times, respectively, the maximum recommended daily intranasal dose in adults on a mcg/m2 basis).

There are no adequate and well-controlled studies in pregnant women. Fluticasone propionate should be used during pregnancy only if the potential benefit justifies the potential risk to the fetus.

Experience with oral corticosteroids since their introduction in pharmacologic, as opposed to physiologic, doses suggests that rodents are more prone to teratogenic effects from corticosteroids than humans. In addition, because there is a natural increase in corticosteroid production during pregnancy, most women will require a lower exogenous corticosteroid dose and many will not need corticosteroid treatment during pregnancy.

Nursing Mothers

It is not known whether fluticasone propionate is excreted in human breast milk. However, other corticosteroids have been detected in human milk. Subcutaneous administration to lactating rats of 10 mcg/kg of tritiated fluticasone propionate (less than the maximum recommended daily intranasal dose in adults on a mcg/m2 basis) resulted in measurable radioactivity in the milk. Since there are no data from controlled trials on the use of intranasal fluticasone propionate by nursing mothers, caution should be exercised when Fluticasone Propionate Nasal Spray, USP is administered to a nursing woman.

Pediatric Use

Six hundred fifty (650) patients aged 4 to 11 years and 440 patients aged 12 to 17 years were studied in US clinical trials with Fluticasone Propionate Nasal Spray, USP. The safety and effectiveness of Fluticasone Propionate Nasal Spray, USP in children below 4 years of age have not been established.

Controlled clinical studies have shown that intranasal corticosteroids may cause a reduction in growth velocity in pediatric patients. This effect has been observed in the absence of laboratory evidence of HPA axis suppression, suggesting that growth velocity is a more sensitive indicator of systemic corticosteroid exposure in pediatric patients than some commonly used tests of HPA axis function. The long-term effects of this reduction in growth velocity associated with intranasal corticosteroids, including the impact on final adult height, are unknown. The potential for "catch-up" growth following discontinuation of treatment with intranasal corticosteroids has not been adequately studied. The growth of pediatric patients receiving intranasal corticosteroids, including Fluticasone Propionate Nasal Spray, USP should be monitored routinely (e.g., via stadiometry). The potential growth effects of prolonged treatment should be weighed against the clinical benefits obtained and the risks/benefits of treatment alternatives. To minimize the systemic effects of intranasal corticosteroids, including Fluticasone Propionate Nasal Spray, USP, each patient should be titrated to the lowest dose that effectively controls his/her symptoms.

A 1-year placebo-controlled clinical growth study was conducted in 150 pediatric patients (ages 3 to 9 years) to assess the effect of Fluticasone Propionate Nasal Spray, USP (single daily dose of 200 mcg, the maximum approved dose) on growth velocity. From the primary population of 56 patients receiving Fluticasone Propionate Nasal Spray, USP and 52 receiving placebo, the point estimate for growth velocity with Fluticasone Propionate Nasal Spray, USP was 0.14 cm/year lower than that noted with placebo (95% confidence interval ranging from 0.54 cm/year lower than placebo to 0.27 cm/year higher than placebo). Thus, no statistically significant effect on growth was noted compared to placebo. No evidence of clinically relevant changes in HPA axis function or bone mineral density was observed as assessed by 12-hour urinary cortisol excretion and dual-energy x-ray absorptiometry, respectively.

The potential for Fluticasone Propionate Nasal Spray, USP to cause growth suppression in susceptible patients or when given at higher doses cannot be ruled out.

Geriatric Use

A limited number of patients 65 years of age and older (n = 129) or 75 years of age and older (n = 11) have been treated with Fluticasone Propionate Nasal Spray, USP in US and non-US clinical trials. While the number of patients is too small to permit separate analysis of efficacy and safety, the adverse reactions reported in this population were similar to those reported by younger patients.

ADVERSE REACTIONS SECTION

In controlled US studies, more than 3,300 patients with seasonal allergic, perennial allergic, or perennial nonallergic rhinitis received treatment with intranasal fluticasone propionate. In general, adverse reactions in clinical studies have been primarily associated with irritation of the nasal mucous membranes, and the adverse reactions were reported with approximately the same frequency by patients treated with the vehicle itself. The complaints did not usually interfere with treatment. Less than 2% of patients in clinical trials discontinued because of adverse events; this rate was similar for vehicle placebo and active comparators.

Systemic corticosteroid side effects were not reported during controlled clinical studies up to 6 months' duration with Fluticasone Propionate Nasal Spray, USP. If recommended doses are exceeded, however, or if individuals are particularly sensitive or taking Fluticasone Propionate Nasal Spray, USP in conjunction with administration of other corticosteroids, symptoms of hypercorticism, e.g., Cushing syndrome, could occur.

The following incidence of common adverse reactions (>3%, where incidence in fluticasone propionate-treated subjects exceeded placebo) is based upon 7 controlled clinical trials in which 536 patients (57 girls and 108 boys aged 4 to 11 years, 137 female and 234 male adolescents and adults) were treated with Fluticasone Propionate Nasal Spray, USP 200 mcg once daily over 2 to 4 weeks and 2 controlled clinical trials in which 246 patients (119 female and 127 male adolescents and adults) were treated with Fluticasone Propionate Nasal Spray, USP 200 mcg once daily over 6 months. Also included in the table are adverse events from 2 studies in which 167 children (45 girls and 122 boys aged 4 to 11 years) were treated with Fluticasone Propionate Nasal Spray, USP 100 mcg once daily for 2 to 4 weeks.

Overall Adverse Experiences With >3% Incidence on Fluticasone Propionate in Controlled Clinical Trials With Fluticasone Propionate Nasal Spray, USP in Patients ≥4 Years With Seasonal or Perennial Allergic Rhinitis
Adverse Experience | Vehicle Placebo (n = 758) % | Fluticasone Propionate 100 mcg Once Daily (n = 167) % | Fluticasone Propionate 200 mcg Once Daily (n = 782) %
Headache | 14.6 | 6.6 | 16.1
Pharyngitis | 7.2 | 6.0 | 7.8
Epistaxis | 5.4 | 6.0 | 6.9
Nasal burning/nasal irritation | 2.6 | 2.4 | 3.2
Nausea/vomiting | 2.0 | 4.8 | 2.6
Asthma symptoms | 2.9 | 7.2 | 3.3
Cough | 2.8 | 3.6 | 3.8

Other adverse events that occurred in ≤3% but ≥1% of patients and that were more common with fluticasone propionate (with uncertain relationship to treatment) included: blood in nasal mucus, runny nose, abdominal pain, diarrhea, fever, flu-like symptoms, aches and pains, dizziness, bronchitis.

Observed During Clinical Practice

In addition to adverse events reported from clinical trials, the following events have been identified during postapproval use of intranasal fluticasone propionate in clinical practice. Because they are reported voluntarily from a population of unknown size, estimates of frequency cannot be made. These events have been chosen for inclusion due to either their seriousness, frequency of reporting, or causal connection to fluticasone propionate or a combination of these factors.

General: Hypersensitivity reactions, including angioedema, skin rash, edema of the face and tongue, pruritus, urticaria, bronchospasm, wheezing, dyspnea, and anaphylaxis/anaphylactoid reactions, which in rare instances were severe.

Ear, Nose, and Throat: Alteration or loss of sense of taste and/or smell and, rarely, nasal septal perforation, nasal ulcer, sore throat, throat irritation and dryness, cough, hoarseness, and voice changes.

Eye: Dryness and irritation, conjunctivitis, blurred vision, glaucoma, increased intraocular pressure, and cataracts.

Cases of growth suppression have been reported for intranasal corticosteroids, including fluticasone propionate (see PRECAUTIONS: Pediatric Use).

OVERDOSAGE SECTION

Chronic overdosage may result in signs/symptoms of hypercorticism (see PRECAUTIONS). Intranasal administration of 2 mg (10 times the recommended dose) of fluticasone propionate twice daily for 7 days to healthy human volunteers was well tolerated. Single oral doses up to 16 mg have been studied in human volunteers with no acute toxic effects reported. Repeat oral doses up to 80 mg daily for 10 days in volunteers and repeat oral doses up to 10 mg daily for 14 days in patients were well tolerated. Adverse reactions were of mild or moderate severity, and incidences were similar in active and placebo treatment groups. Acute overdosage with this dosage form is unlikely since 1 bottle of Fluticasone Propionate Nasal Spray, USP contains approximately 8 mg of fluticasone propionate.

The oral and subcutaneous median lethal doses in mice and rats were >1,000 mg/kg (>20,000 and >41,000 times, respectively, the maximum recommended daily intranasal dose in adults and >10,000 and >20,000 times, respectively, the maximum recommended daily intranasal dose in children on a mg/m2 basis).

DOSAGE & ADMINISTRATION SECTION

Patients should use Fluticasone Propionate Nasal Spray, USP at regular intervals for optimal effect.

Adults

The recommended starting dosage in adults is 2 sprays (50 mcg of fluticasone propionate each) in each nostril once daily (total daily dose, 200 mcg). The same dosage divided into 100 mcg given twice daily (e.g., 8 a.m. and 8 p.m.) is also effective. After the first few days, patients may be able to reduce their dosage to 100 mcg (1 spray in each nostril) once daily for maintenance therapy. Some patients (12 years of age and older) with seasonal allergic rhinitis may find as-needed use of 200 mcg once daily effective for symptom control (see Clinical Trials). Greater symptom control may be achieved with scheduled regular use.

Adolescents and Children (4 Years of Age and Older)

Patients should be started with 100 mcg (1 spray in each nostril once daily). Patients not adequately responding to 100 mcg may use 200 mcg (2 sprays in each nostril). Once adequate control is achieved, the dosage should be decreased to 100 mcg (1 spray in each nostril) daily.

The maximum total daily dosage should not exceed 2 sprays in each nostril (200 mcg/day). (See Individualization of Dosage and Clinical Trials sections.)

Fluticasone Propionate Nasal Spray, USP is not recommended for children under 4 years of age.

Directions for Use

Illustrated patient's instructions for proper use accompany each package of Fluticasone Propionate Nasal Spray, USP.

HOW SUPPLIED SECTION

Fluticasone Propionate Nasal Spray, USP 50 mcg is supplied in an amber glass bottle fitted with a white metering atomizing pump, white nasal adapter, and transparent dust cap in a box of 1 (NDC 60432-264-15) with patient's instructions for use. Each bottle contains a net fill weight of 16 g and will provide 120 actuations. Each actuation delivers 50 mcg of fluticasone propionate in 100 mg of formulation through the nasal adapter. The correct amount of medication in each spray cannot be assured after 120 sprays even though the bottle is not completely empty. The bottle should be discarded when the labeled number of actuations has been used.

Store between 4° and 30°C (39° and 86°F).